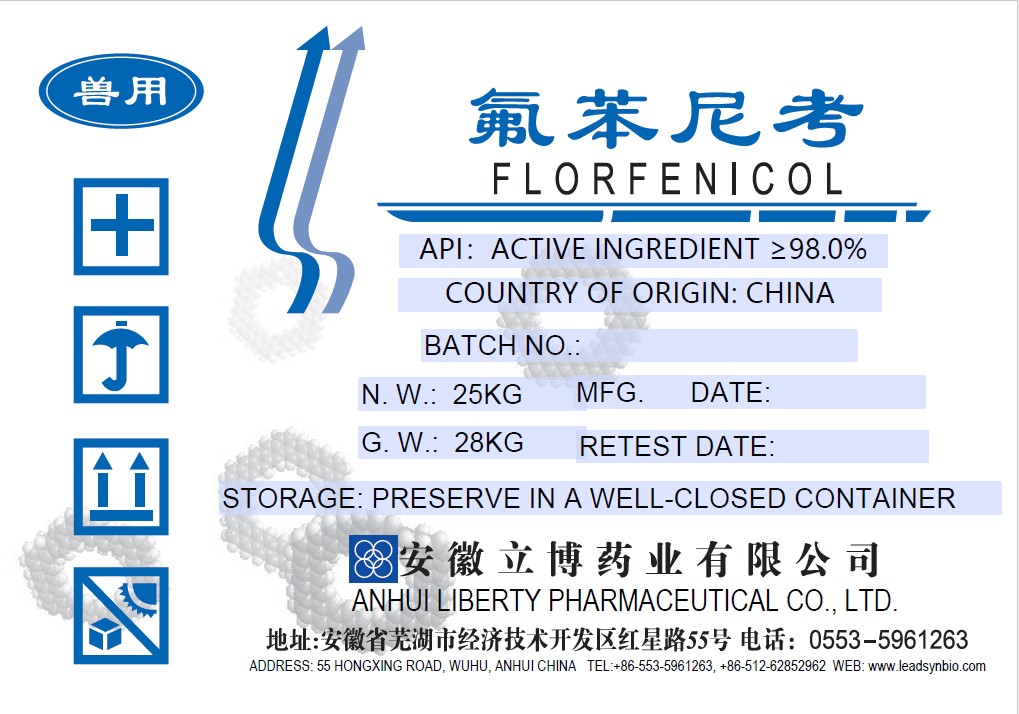 DRUG LABEL: FLORFENICOL
NDC: 86221-001 | Form: POWDER
Manufacturer: Anhui Liberty Pharmaceutical Co., Ltd.
Category: other | Type: BULK INGREDIENT - ANIMAL DRUG
Date: 20250416

ACTIVE INGREDIENTS: FLORFENICOL 1 kg/1 kg

Apply for NDC for Florfenicol API

Florfenicol label